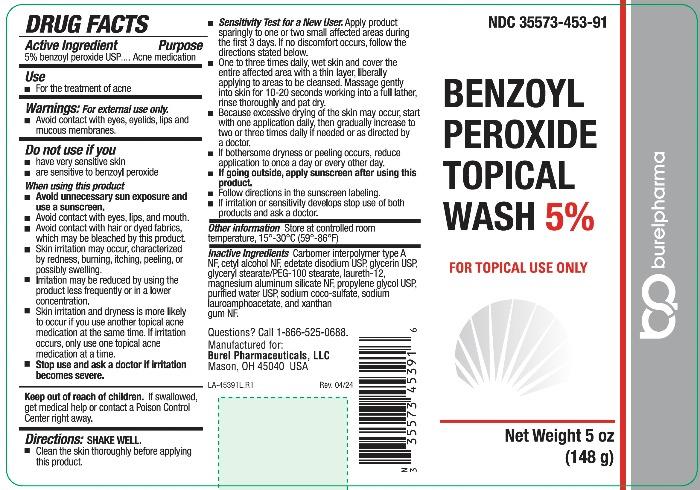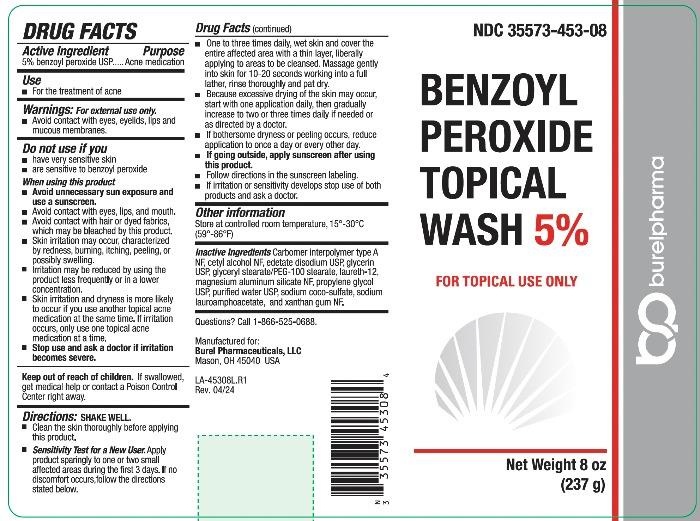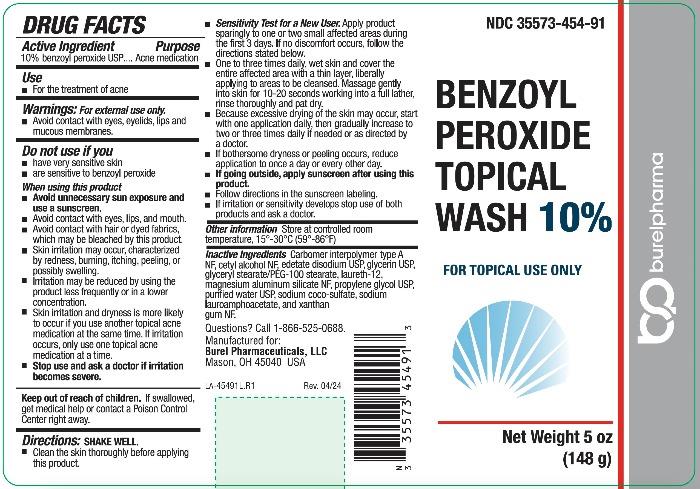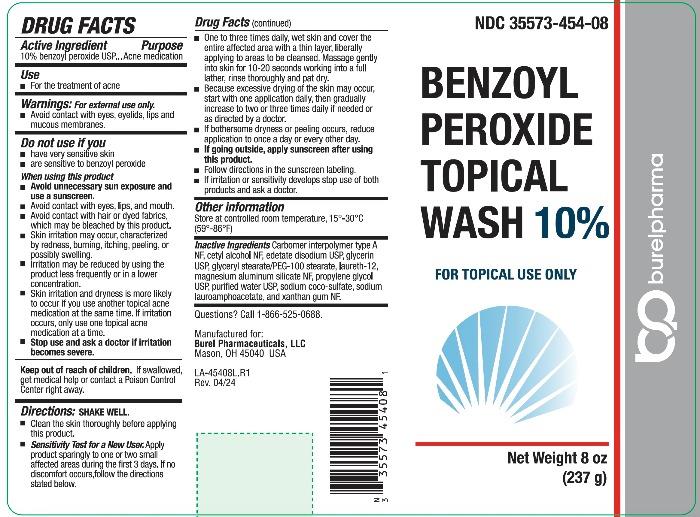 DRUG LABEL: Benzoyl Peroxide
NDC: 35573-453 | Form: LIQUID
Manufacturer: Burel Pharmaceuticals, LLC
Category: otc | Type: HUMAN OTC DRUG LABEL
Date: 20240424

ACTIVE INGREDIENTS: Benzoyl Peroxide 50 mg/1 mL
INACTIVE INGREDIENTS: CARBOMER INTERPOLYMER TYPE A (ALLYL SUCROSE CROSSLINKED); cetyl alcohol; edetate disodium; glycerin; GLYCERYL STEARATE/PEG-100 STEARATE; laureth-12; magnesium aluminum silicate; propylene glycol; water; sodium coco-sulfate; sodium lauroamphoacetate; xanthan gum

BENZOYL PEROXIDE TOPICAL WASH

DRUG FACTS

Active Ingredient

benzoyl peroxide USP, 5% or 10%

Purpose

Acne medication

Use

- For the treatment of acne

Warnings:

For external use only.

- Avoid contact with eyes, eyelids, lips and mucous membranes.

Do not use if you

- have very sensitive skin
- are sensitive to benzoyl peroxide

When using this product

- Avoid unnecessary sun exposure and use a sunscreen.
- Avoid contact with eyes, lips, and mouth.
- Avoid contact with hair or dyed fabrics, which may be bleached by this product.
- Skin irritation may occur, characterized by redness, burning, itching, peeling, or possibly swelling.
- Irritation may be reduced by using the product less frequently or in a lower concentration.
- Skin irritation and dryness is more likely to occur if you use another topical acne medication at the same time. If irritation occurs, only use one topical acne medication at a time.
- Stop use and ask a doctor if irritation becomes severe.

Keep out of reach of children

If swallowed, get medical help or contact a Poison Control Center right away.

Directions

SHAKE WELL.

- Clean the skin thoroughly before applying this product.
- Sensitivity Test for a New User. Apply product sparingly to one or two small affected areas during the first 3 days. If no discomfort occurs,follow the directions stated below.
- One to three times daily, wet skin and cover the entire affected area with a thin layer, liberally applying to areas to be cleansed. Massage gently into skin for 10-20 seconds working into a full lather, rinse thoroughly and pat dry.
- Because excessive drying of the skin may occur, start with one application daily, then gradually increase to two or three times daily if needed or as directed by a doctor.
- If bothersome dryness or peeling occurs, reduce application to once a day or every other day.
- If going outside, apply sunscreen after using this product.
- Follow directions in the sunscreen labeling.
- If irritation or sensitivity develops stop use of both products and ask a doctor.

Other information

Store at controlled room temperature, 15° - 30°C (59° - 86°F)

Inactive Ingredients

Carbomer interpolymer type A NF, cetyl alcohol NF, edetate disodium USP, glycerin USP, glyceryl stearate/PEG-100 stearate, laureth-12, magnesium aluminum silicate NF, propylene glycol USP, purified water USP, sodium coco-sulfate, sodium lauroamphoacetate, and xanthan gum NF.

Questions? Call 1-866-525-0688
Manufactured for:
Burel Pharmaceuticals, LLC
Mason, OH 45040 USA
Rev. 04/24

PRINCIPAL DISPLAY PANEL - 5% 5oz (148 g) Bottle Label

NDC 35573-453-91

BENZOYL
PEROXIDE
TOPICAL
WASH 5%

FOR TOPICAL USE ONLY

Net Weight 5 oz
(148 g)

burelpharma

PRINCIPAL DISPLAY PANEL - 5% 8oz (237 g) Bottle Label

NDC 35573-453-08

BENZOYL
PEROXIDE
TOPICAL
WASH 5%

FOR TOPICAL USE ONLY

Net Weight 8 oz
(237 g)

burelpharma

PRINCIPAL DISPLAY PANEL - 10% 5oz (148 g) Bottle Label

NDC 35573-454-91

BENZOYL
PEROXIDE
TOPICAL
WASH 10%

FOR TOPICAL USE ONLY

Net Weight 5 oz
(148 g)

burelpharma

PRINICIPAL DISPLAY PANEL - 10% 8oz (237 g) Bottle Label

NDC 35573-454-08

BENZOYL
PEROXIDE
TOPICAL
WASH 10%

FOR TOPICAL USE ONLY

Net Weight 8 oz
(237 g)

burelpharma